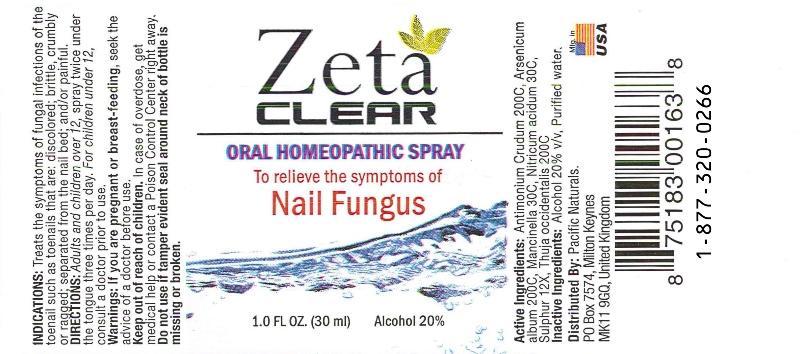 DRUG LABEL: Zeta Clear
NDC: 43695-0005 | Form: LIQUID
Manufacturer: Pacific Naturals
Category: homeopathic | Type: HUMAN OTC DRUG LABEL
Date: 20150305

ACTIVE INGREDIENTS: ANTIMONY TRISULFIDE 200 [hp_C]/1 mL; ARSENIC TRIOXIDE 200 [hp_C]/1 mL; HIPPOMANE MANCINELLA FRUITING LEAFY TWIG 30 [hp_C]/1 mL; NITRIC ACID 30 [hp_C]/1 mL; SULFUR 12 [hp_X]/1 mL; THUJA OCCIDENTALIS LEAF 200 [hp_C]/1 mL
INACTIVE INGREDIENTS: WATER; ALCOHOL

Drug Facts:

ACTIVE INGREDIENTS:

Antimonium Crudum 200C, Arsenicum Album 200C, Mancinella 30C, Nitricum Acidum 30C, Sulphur 12X, Thuja Occidentalis 200C

INDICATIONS:

Treats the symptoms of funal infections of the toenail such as toenails that are: discolored; brittle, crumbly or ragged; separated from the nail bed; and or painful.

WARNINGS:

If you are pregnant or breast-feeding, seek the advice of a doctor before use.

Keep out of reach of children. In case of overdose, get medical help or contact a Poison Control Center right away.

Do not use if tamper evident seal around neck of bottle is missing or broken.

DIRECTIONS:

Adults and children over 12, spray twice under the tongue three times per day.

For children under 12, consult a doctor prior to use.

INACTIVE INGREDIENTS:

Alcohol 20%, Purified Water

KEEP OUT OF REACH OF CHILDREN:

In case of overdose, get medical help or contact a Poison Control Center right away.

INDICATIONS:

Treats the symptoms of funal infections of the toenail such as toenails that are: discolored; brittle, crumbly or ragged; separated from the nail bed; and or painful.

QUESTIONS:

Distributed By: Pacific Naturals

2049 N. Lincoln St. Burbank, CA 91504

1-800-756-4120 Mon-Fri 9AM to 5 PM PST

PACKAGE LABEL DISPLAY:

Zeta

CLEAR

ORAL HOMEOPATHIC SPRAY

To relieve the symptoms of

Nail Fungus

1.0 FL OZ (30 ml)